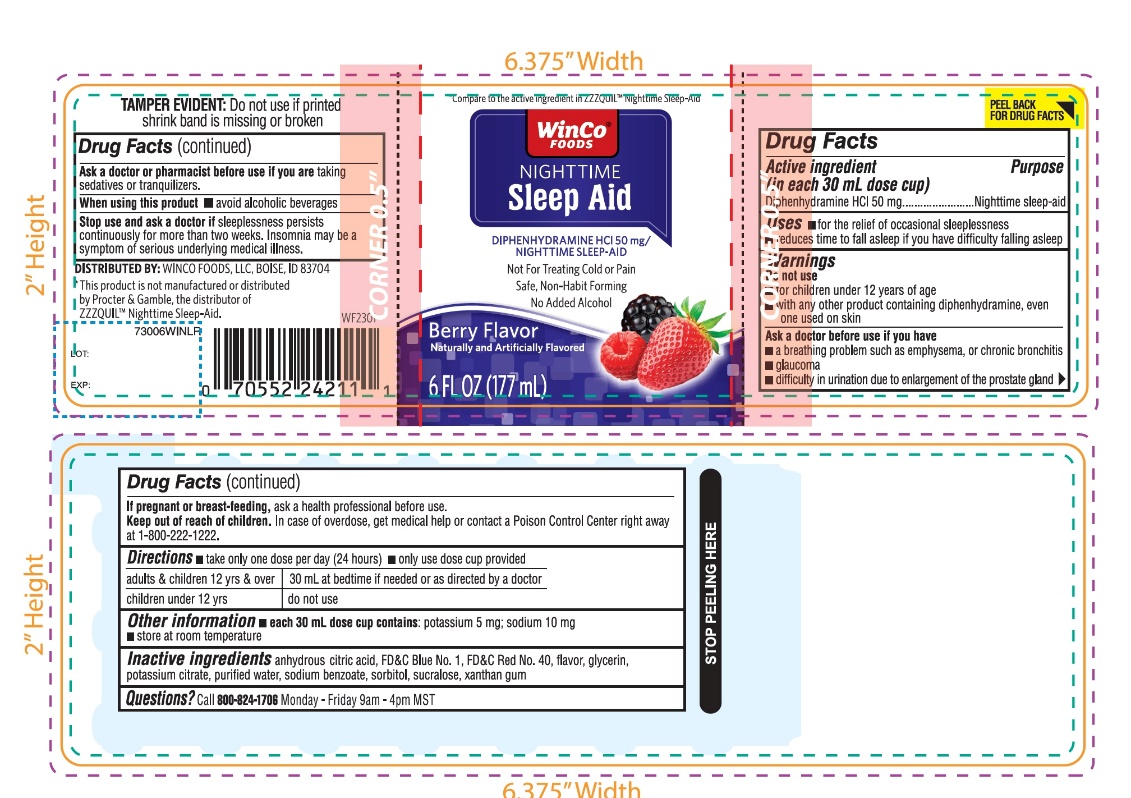 DRUG LABEL: Nighttime Sleep Aid

NDC: 67091-630 | Form: LIQUID
Manufacturer: WINCO FOODS, LLC
Category: otc | Type: HUMAN OTC DRUG LABEL
Date: 20251202

ACTIVE INGREDIENTS: DIPHENHYDRAMINE HYDROCHLORIDE 50 mg/30 mL
INACTIVE INGREDIENTS: ANHYDROUS CITRIC ACID; FD&C BLUE NO. 1; FD&C RED NO. 40; GLYCERIN; POTASSIUM CITRATE; WATER; SODIUM BENZOATE; SORBITOL; SUCRALOSE; XANTHAN GUM

WINCO®Nighttime Sleep-Aid

Drug Facts

Active ingredient (in each 30 mL dose cup)

Diphenhydramine HCl 50 mg

Purpose

Nighttime sleep-aid

Uses

- for the relief of occasional sleeplessness
- reduces time to fall asleep if you have difficulty falling asleep

Warnings

Do not use

- for children under 12 years of age
- with any other product containing diphenhydramine, even one used on skin

Ask a doctor before use if you have

- a breathing problem such as emphysema, or chronic bronchitis
- glaucoma
- difficulty in urination due to enlargement of the prostate gland

Ask a doctor or pharmacist before use if you aretaking sedatives or tranquilizers.

When using this product

- avoid alcoholic beverages

Stop use and ask a doctor ifsleeplessness persists continuously for more than two weeks. Insomnia may be a symptom of serious underlying medical illness.

PREGNANCY OR BREAST FEEDING

If pregnant or breast-feeding, ask a health professional before use.

Keep out of reach of children.

Overdose warning:

In case of overdose, get medical help or contact a Poison Control Center right away at 1-800-222-1222.

Directions

- take only one dose per day (24 hours)
- only use cup provided.

adults & children 12yrs & over | 30 mL at bed time if needed or as directed by a doctor
Children under 12 yrs | do not use

Other information

- each 30 mL dose contains:potassium 5 mg, sodium 10 mg
- store at room temperature

Inactive ingredients

anhydrous citric acid, FD&C Blue No. 1, FD&C Red No. 40, flavor, glycerin, potassium citrate, purified water, sodium benzoate, sorbitol, sucralose, xanthan gum.

PRINCIPAL DISPLAY PANEL

NDC 67091-630-06

Compare to the active ingredient in ZzzQuil™ Nighttime Sleep-Aid*

Nighttime Sleep-Aid

Diphenhydramine HCl

Non-Habit Forming

Makes you fall asleep fast

BERRY FLAVOR

Naturally and Artificially Flavored

No added alcohol

Not for Pain. Not for Colds.

Just for Sleep

6 FL OZ (177 mL)

TAMPER EVIDENT: DO NOT USE IF PRINTED SHRINK BAND IS MISSING OR BROKEN

*This product is not manufactured or distributed by Procter & Gamble, the distributor of ZzzQuil™ Nighttime Sleep-Aid.